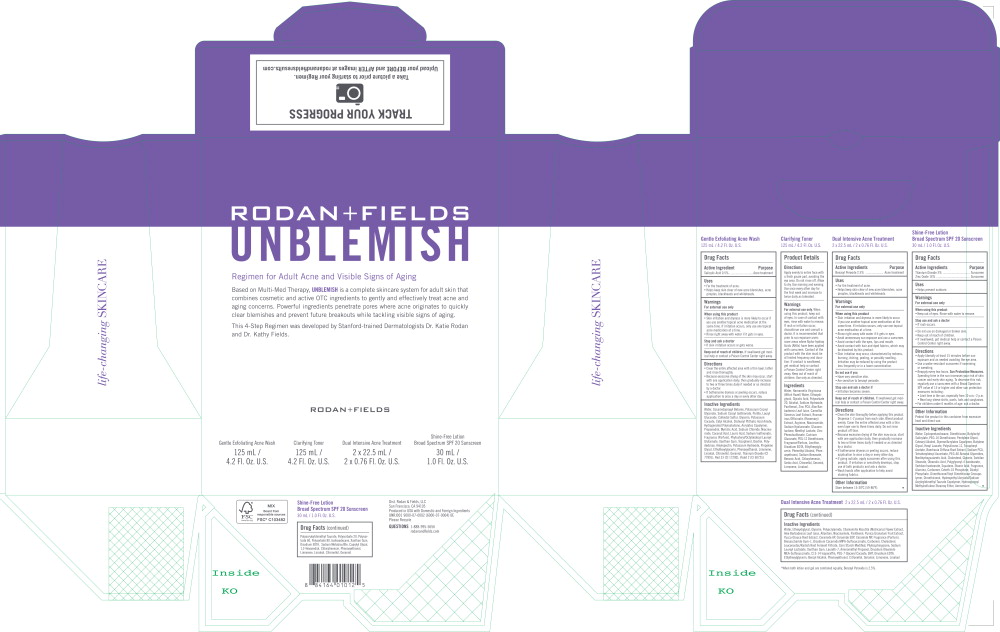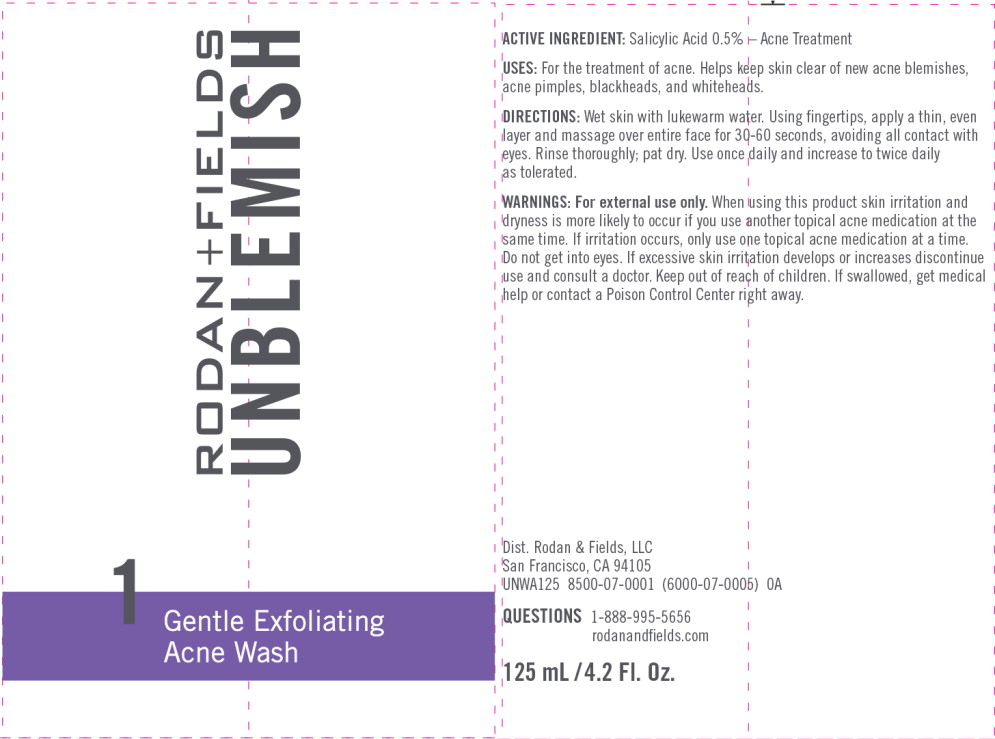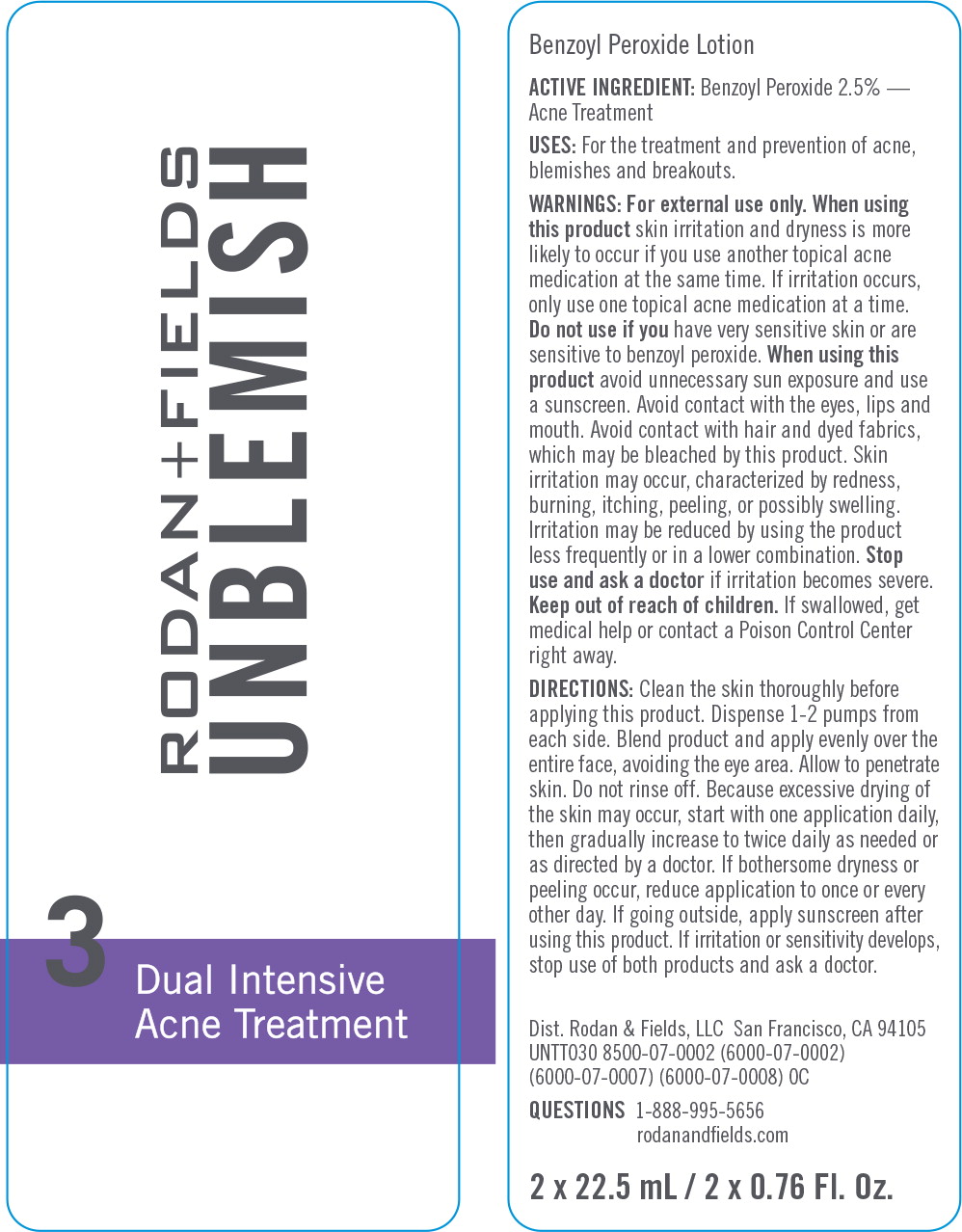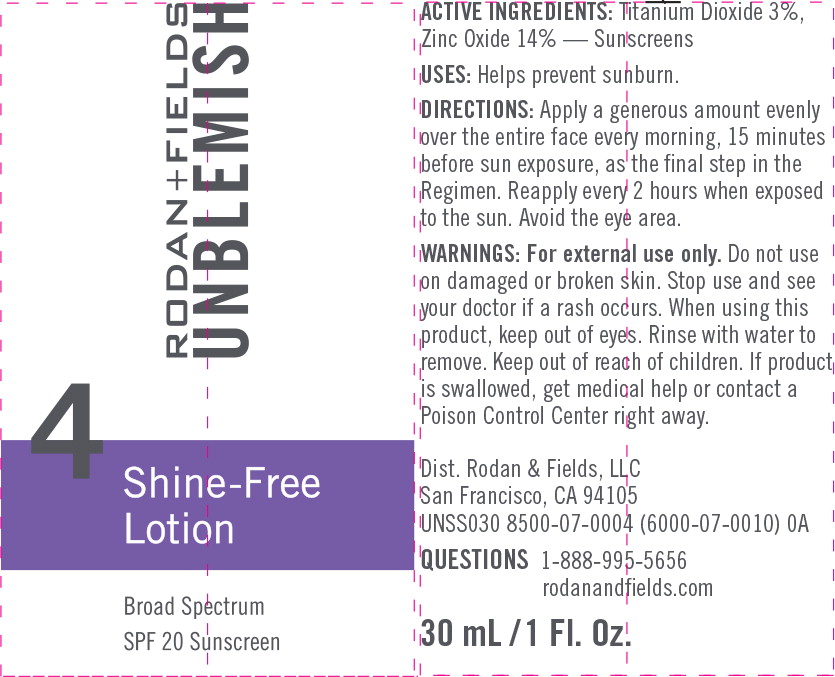 DRUG LABEL: UNBLEMISH Regimen for Acne, Blemishes and Breakouts
NDC: 14222-2100 | Form: KIT | Route: TOPICAL
Manufacturer: Rodan & Fields
Category: otc | Type: HUMAN OTC DRUG LABEL
Date: 20190213

ACTIVE INGREDIENTS: SALICYLIC ACID 0.005 g/1 mL; BENZOYL PEROXIDE 0.025 g/1 mL; TITANIUM DIOXIDE 0.03 g/1 mL; ZINC OXIDE 0.14 g/1 mL
INACTIVE INGREDIENTS: WATER; COCAMIDOPROPYL BETAINE; POTASSIUM COCOYL GLYCINATE; SODIUM COCOYL ISETHIONATE; PERLITE; LAURYL GLUCOSIDE; SULFUR; GLYCERIN; POTASSIUM COCOATE; CETYL ALCOHOL; DISTEARYL PHTHALAMIC ACID; HYDROGENATED POLYBUTENE (1300 MW); PROPANEDIOL; MYRISTIC ACID; .BETA.-CITRONELLOL, (R)-; AMYLOPECTIN; COCONUT ACID; D&C RED NO. 33; D&C VIOLET NO. 2; ETHYLHEXYLGLYCERIN; GERANIOL; ICODEXTRIN; LAURIC ACID; LIMONENE, (+)-; LINALOOL, (+/-)-; NIACINAMIDE; PHENOXYETHANOL; PHYTOSTERYL/OCTYLDODECYL LAUROYL GLUTAMATE; POLYDEXTROSE; POTASSIUM HYDROXIDE; PROPYLENE GLYCOL; SODIUM CHLORIDE; SODIUM ISETHIONATE; TITANIUM DIOXIDE; TOCOPHEROL; XANTHAN GUM; WATER; DIETHYLENE GLYCOL MONOETHYL ETHER; GLYCERIN; POLYACRYLAMIDE (10000 MW); .BETA.-CITRONELLOL, (R)-; ALLANTOIN; ALOE VERA LEAF; AMINOMETHYLPROPANOL; BENZYL ALCOHOL; BIOSACCHARIDE GUM-1; BUTYLATED HYDROXYTOLUENE; C13-14 ISOPARAFFIN; CARBOXYPOLYMETHYLENE; CERAMIDE 1; CERAMIDE AP; CERAMIDE NP; CHOLESTEROL; DISODIUM OLEAMIDO MONOETHANOLAMINE SULFOSUCCINATE; EDETATE DISODIUM ANHYDROUS; ETHYLHEXYLGLYCERIN; GERANIOL; LAURETH-7; LEUCONOSTOC/RADISH ROOT FERMENT FILTRATE; LIMONENE, (+)-; LINALOOL, (+/-)-; MATRICARIA CHAMOMILLA FLOWERING TOP; NIACINAMIDE; PANTHENOL; PEG-7 GLYCERYL COCOATE; PHENOXYETHANOL; PHYTOSPHINGOSINE; POMEGRANATE; SODIUM LAUROYL LACTYLATE; STARCH, CORN; XANTHAN GUM; YUCCA GLAUCA ROOT; WATER; CYCLOMETHICONE 5; DIMETHICONE; BUTYLOCTYL SALICYLATE; PEG-10 DIMETHICONE (600 CST); PENTYLENE GLYCOL; CETOSTEARYL ALCOHOL; BUTYLENE GLYCOL; HEXYL LAURATE; .ALPHA.-TOCOPHEROL ACETATE, DL-; 1,2-HEXANEDIOL; ALUMINUM OXIDE; BOERHAVIA DIFFUSA ROOT; CAPRYLYL GLYCOL; CARBOXYPOLYMETHYLENE; CETETH-10 PHOSPHATE; CHLORPHENESIN; CHOLESTEROL; DIHEXADECYL PHOSPHATE; DIMETHICONE/VINYL DIMETHICONE CROSSPOLYMER (SOFT PARTICLE); DIMETHICONOL (600000 CST); EDETATE DISODIUM ANHYDROUS; GLYCERIN; GLYCERYL MONOSTEARATE; ISOHEXADECANE; OLEANOLIC ACID; PEG-100 STEARATE; PEG-60 ALMOND GLYCERIDES; PHENOXYETHANOL; POLYGLYCERYL-4 ISOSTEARATE; POLYSORBATE 20; POLYSORBATE 60; POLYSORBATE 80; SODIUM HYDROXIDE; SODIUM METABISULFITE; SODIUM PYRROLIDONE CARBOXYLATE; SORBITAN ISOSTEARATE; SQUALANE; STEARIC ACID; TETRAHEXYLDECYL ASCORBATE; XANTHAN GUM; LIMONENE, (+)-; LINALOOL, (+/-)-; .BETA.-CITRONELLOL, (R)-; GERANIOL

Gentle Exfoliating Acne Wash

125mL/4.2 Fl. Oz.U.S.

Drug Facts

Active Ingredient

Salicylic Acid 0.5%

Purpose

Acne treatment

Uses

- For the treatment of acne.
- Helps keep skin clear of new acne blemishes, acne pimples, blackheads and whiteheads.

Warnings

For external use only

When using this product

- Skin irritation and dryness is more likely to occur if you use another topical acne medication at the same time. If irritation occurs, only use one topical acne medication at a time.
- Rinse right away with water if it gets in eyes.

Stop and ask a doctor

- If skin irritation occurs or gets worse.

Keep out of reach of children. If swallowed get medical help or contact a Poison Control Center right away.

Directions

- Cover the entire affected area with a thin layer, lather and rinse thoroughly.
- Because excessive drying of the skin may occur, start with one application daily, then gradually increase to two or three times daily if needed or as directed by a doctor.
- If bothersome dryness or peeling occurs, reduce application to once a day or every other day.

Inactive Ingredients

Water, CocamidopropyI Betaine, Potassium Cocoyl Glycinate, Sodium Cocoyl Isethionate, Perlite, Lauryl Glucoside, Colloidal Sulfur, Glycerin, Potassium Cocoate, Cetyl Alcohol, Distearyl Phthalic Acid Amide, Hydrogenated Polyisobutene, Acrylates Copolymer, Propanediol, Myristic Acid, Sodium Chloride, Niacinamide, Coconut Acid, Lauric Acid, Sodium Isethionate, Fragrance (Parfum), Phytosteryl/OctyIdodecyl Lauroyl Glutamate, Xanthan Gum, Tocopherol, Dextrin, Polydextrose, AmyIopectin, Potassium Hydroxide, Propylene Glycol, Ethylhexylglycerin, Phenoxyethanol, Limonene, Linalool, Citronellol, Geraniol, Titanium Dioxide (Cl 77891), Red 33 (Cl 17200), Violet 2 (Cl 60725)

Dual Intensive Acne Treatment

2 x 22.5mL/ 2 x 0.76 Fl. Oz. U.S.

Drug Facts

Active Ingredients

Benzoyl Peroxide 2.5%

Purpose

Acne treatment

Uses

- For the treatment of acne.
- Helps keep skin clear of new acne blemishes, acne pimples, blackheads and whiteheads.

Warnings

For external use only

When using this product

- Skin irritation and dryness is more likely to occur if you use another topical acne medication at the same time. If irritation occurs, only use one topical acne medication at a time.
- Rinse right away with water if it gets in eyes.
- Avoid unnecessary sun exposure and use a sunscreen.
- Avoid contact with the eyes, lips and mouth.
- Avoid contact with hair and dyed fabrics, which may be bleached by this product.
- Skin irritation may occur, characterized by redness, burning, itching, peeling, or possibly swelling. Irritation may be reduced by using the product less frequently or in a lower concentration.

Do not use if you

- Have very sensitive skin.
- Are sensitive to benzoyl peroxide.

Stop use and ask a doctor if

- Irritation becomes severe.

Keep out of reach of children. If swallowed get medical help or contact a Poison Control Center right away.

Directions

- Clean the skin thoroughly before applying this product. Dispense 1-2 pumps from each side. Blend product evenly. Cover the entire affected area with a thin even layer one to three times daily. Do not rinse product off face.
- Because excessive drying of the skin may occur, start with one application daily, then gradually increase to two or three times daily if needed or as directed by a doctor.
- If bothersome dryness or peeling occurs, reduce application to once a day or every other day.
- If going outside, apply sunscreen after using this product. If irritation or sensitivity develops, stop use of both products and ask a doctor.
- Wash hands after application to help avoid staining fabrics.

Other Information

Store between 15-30°C (59-86°F).

Inactive Ingredients

Water, Ethoxydiglycol, Glycerin, Polyacrylamide, Chamomilla Recutita (Matricaria) Flower Extract, Aloe Barbadensis Leaf Juice, Allantoin, Niacinamide, Panthenol, Punica Granatum Fruit Extract, Yucca Glauca Root Extract, Ceramide AP, Ceramide EOP, Ceramide NP, Fragrance (Parfum), Biosaccharide Gum-1, Disodium Cocamido MlPA-SuIfosuccinate, Carbomer, Cholesterol, Leuconostoc/Radish Root Ferment Filtrate, Corn Starch Modified, Phytosphingosine, Sodium Lauroyl Lactylate, Xanthan Gum, Laureth-7, Aminomethyl Propanol, Disodium Oleamido MEA-Sulfosuccinate, C13-14 Isoparaffin, PEG-7 Glyceryl Cocoate, BHT, Disodium EDTA, Ethylhexylglycerin, Benzyl Alcohol, Phenoxyethanol, Citronellol, Geraniol, Limonene, Linalool

Shine-Free Lotion Broad Spectrum SPF 20 Sunscreen

Drug Facts

Active Ingredients

Titanium Dioxide 3%

Zinc Oxide 14%

Purpose

Sunscreen

Sunscreen

Uses

- Helps prevent sunburn.

Warnings

For external use only

When using this product

- Keep out of eyes. Rinse with water to remove.

Stop use and ask a doctor

- If rash occurs.

- Do not use on damaged or broken skin.

- Keep out of reach of children.
- If swallowed, get medical help or contact a Poison Control Center right away.

Directions

- Apply liberally at least 15 minutes before sun exposure and as needed avoiding the eye area.
- Use a water-resistant sunscreen if swimming or sweating.
- Reapply every two hours. Sun Protection Measures. Spending time in the sun increases your risk of skin cancer and early skin aging. To decrease this risk, regularly use a sunscreen with a Broad Spectrum SPF value of 15 or higher and other sun protection measures including:
- Limit time in the sun, especially from 10 a.m.-2 p.m.
- Wear long-sleeve shirts, pants, hats and sunglasses.
- For children under 6 months of age: ask a doctor.

Other Information

Protect the product in this container from excessive heat and direct sun.

Inactive Ingredients

Water, Cyclopentasiloxane, Dimethicone, Butyloctyl Salicylate, PEG-10 Dimethicone, Pentylene Glycol, Cetearyl Alcohol, Styrene/Acrylates Copolymer, Butylene Glycol, Hexyl Laurate, Polysilicone-11, Tocopheryl Acetate, Boerhavia Diffusa Root Extract, Sodium PCA, Tetrahexyldecyl Ascorbate, PEG-60 Almond Glycerides, Nordihydraguaiaretic Acid, Cholesterol, Glycerin, Sorbitan Stearate, Oleanolic Acid, Polyglyceryl-4 Isostearate, Sorbitan Isostearate, Squalane, Stearic Acid, Fragrance, Alumina, Carbomer, Ceteth-10 Phosphate, Dicetyl Phosphate, Dimethicone/Vinyl Dimethicone Crosspolymer, Dimethiconol, Hydroxyethyl Acrylate/Sodium Acryloyldimethyl Taurate Copolymer, Hydroxypropyl Methylcellulose Stearoxy Ether, Ammonium, Polyacryloyldimethyl Taurate, Polysorbate 20, Polysorbate 60, Polysorbate 80, Isohexadecane, Xanthan Gum, Disodium EDTA, Sodium Metabisulfite, Caprylyl Glycol, 1,2-Hexanediol, Chlorphenesin, Phenoxyethanol, Limonene, Linalool, Citronellol, Geraniol

Principal Display Panel - Kit Label

RODAN+FIELDS

UNBLEMISH

Regimen for Adult Acne and Visible Signs of Aging

Based on Multi-Med Therapy, UNBLEMISH is a complete skincare system for adult skin that combines cosmetics and active OTC ingredients to gently and effectively treat acne and aging concerns. Powerful ingredients penetrate pores where acne originates to quickly clear blemishes and prevent future breakouts while tackling visible signs of aging.

This 4-Step Regimen was developed by Stanford-trained Dermatologist Dr. Katie Rodan and Dr.Kathy Fields.

RODAN+FIELDS

Gentle Exfoliating Acne Wash

125 mL/
4.2 Fl. Oz. U.S.

Clarifying Toner

125 mL/
4.2 Fl. Oz. U.S.

Dual Intensive Acne Treatment

2 x 22.5 mL/
2 x 0.76 Fl. Oz. U.S.

Shine-Free Lotion
Broad Spectrum SPF 20 Sunscreen

30 mL/
1.0 Fl. Oz. U.S.

Principal Display Panel - Gentle Exfoliating Acne Wash Tube Label

RODAN+FIELDS

UNBLEMISH

1 Gentle Exfoliating
Acne Wash

Principal Display Panel - Dual Intensive Acne Treatment Tube Label

RODAN+FIELDS

UNBLEMISH

3 Dual Intensive
Acne Treatment

Principal Display Panel - Shine-Free Lotion Tube Label

RODAN+FIELDS

UNBLEMISH

4 Shine-Free
Lotion

Broad Spectrum

SPF 20 Sunscreen